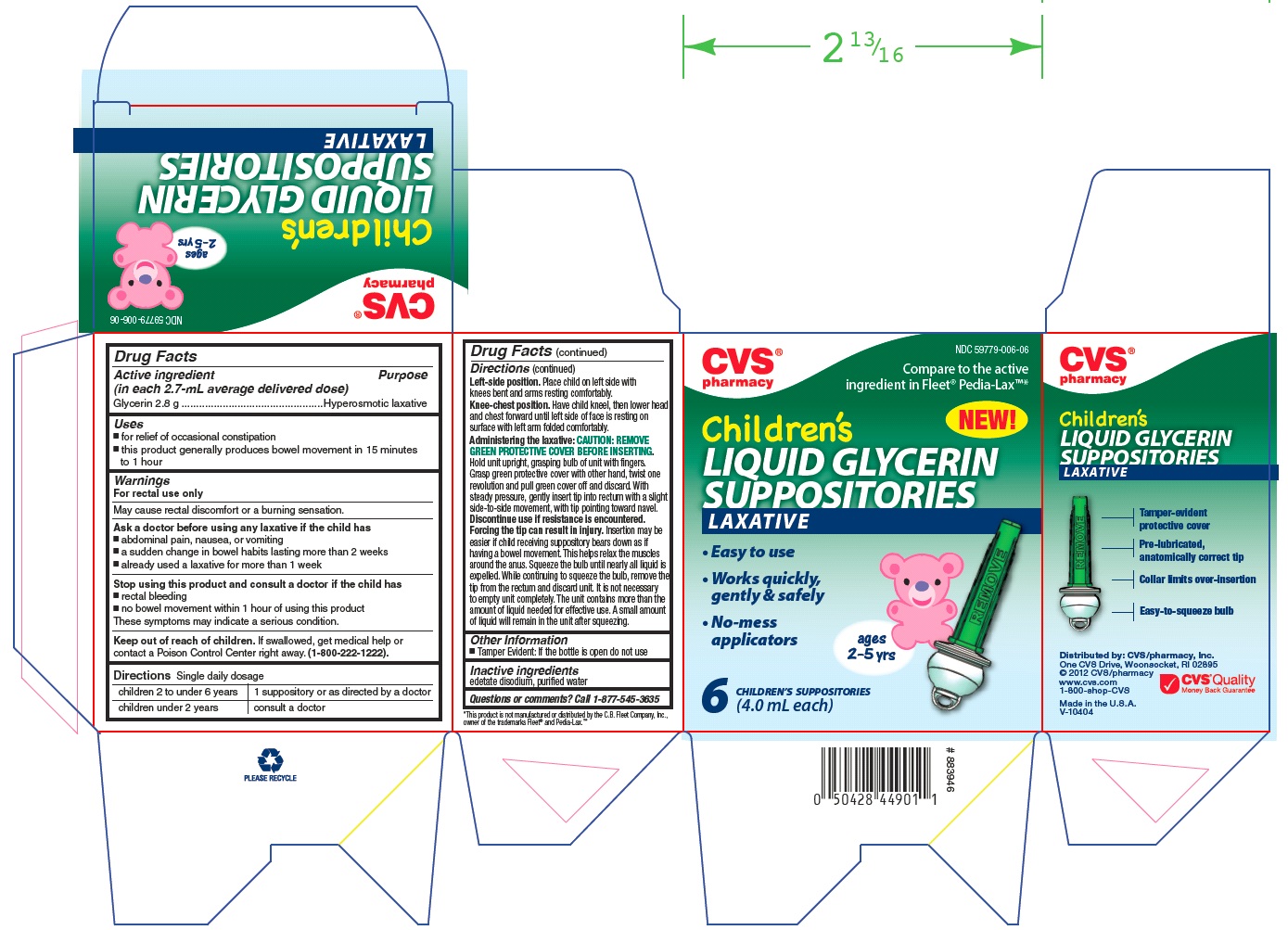 DRUG LABEL: CVS Pharmacy Childrens GLYCERIN SUPPOSITORIES
NDC: 59779-006 | Form: LIQUID
Manufacturer: CVS PHARMACY, INC.
Category: otc | Type: HUMAN OTC DRUG LABEL
Date: 20120210

ACTIVE INGREDIENTS: Glycerin 2.8 g/1 1
INACTIVE INGREDIENTS: EDETATE DISODIUM; WATER

Drug Facts

Active Ingredient (in each 2.7 - mL average delivered dose)

Glycerin 2.8 g.................Hyperosmotic Laxative

Use

- or relief of occasional constipation
- this product generally produes bowel movement in 15 minutes to 1 hour

Warnings

For rectal use only

May cause rectal discomfort or a burning sensation

Ask a doctor before using any laxative if you have

- abdominal pain, nausea, or vomiting
- a sudden change in bowel habits lasting more than 2 weeks
- already used a laxative for more than 1 week

Stop using this product and consult a doctor if you have

- rectal bleeding
- no bowel movement after use of a laxative

These symptoms may indicate a serious condition.

Keep out of reach of children

If swallowed, get medical help or contact a Poison Control Center right away. (1-800-222-1222)

Directions

Single daily dosage

children 2 to under 6 years | 1 suppository or as directed by a doctor
children under 2 years | consult a doctor

Left-side position. Place child on left side with knees bent and arms resting comfortably.
Knee-chest position. Have child kneel, then lower head and chest forward until left side of face is resting on surface with left arm folded comfortably.
Administering the laxative: CAUTION: REMOVE GREEN PROTECTIVE COVER BEFORE INSERTING. Hold unit upright, grasping bulb of unit with fingers. Grasp green protective cover with other hand, twist one revolution and pull green cover off and discard. With steady pressure, gently insert tip into rectum with a slight side-to-side movement, with tip pointing toward navel.
Discontinue use if resistance is encountered. Forcing the tip can result in injury. Insertion may be easier if child receiving suppository bears down as if having a bowel movement. This helps relax the muscles around the anus. Squeeze the bulb until nearly all liquid is expelled. While continuing to squeeze the bulb, remove the tip from the rectum and discard unit. It is not necessary to empty unit completely. The unit contains more than the amount of liquid needed for effective use. A small amount of liquid will remain in the unit after squeezing.

Other Information

- Tamper Evident: If the bottle is open do not use

Inactive Ingredients

edetate disodium, purified water

Questions or comments?

Call 1-877-545-3635